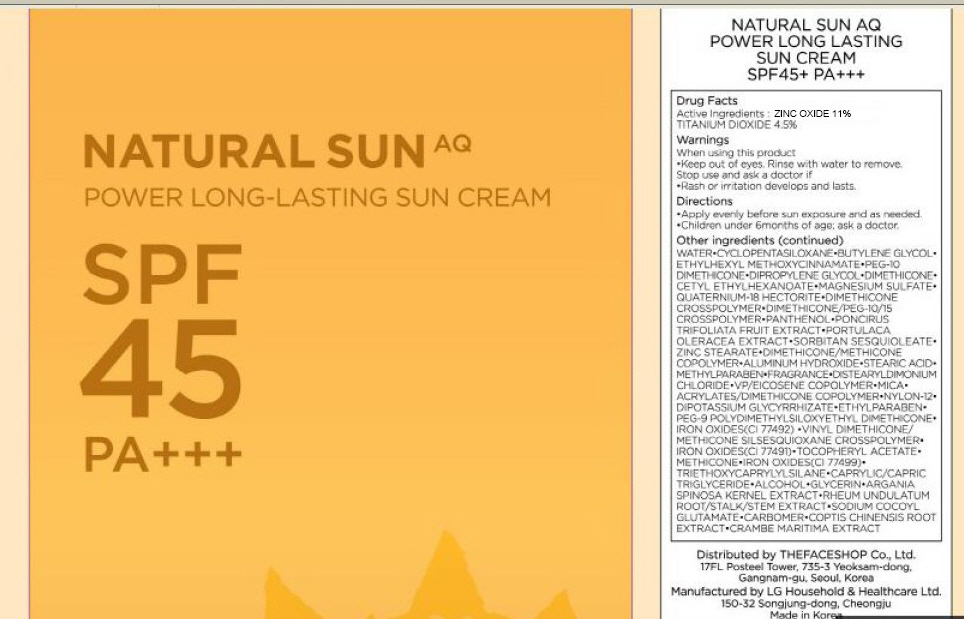 DRUG LABEL: NATURAL SUN AQ POWER LONG LASTING SUN
NDC: 51523-020 | Form: CREAM
Manufacturer: THEFACESHOP CO., LTD.
Category: otc | Type: HUMAN OTC DRUG LABEL
Date: 20100714

ACTIVE INGREDIENTS: ZINC OXIDE 5.5 mL/50 mL; TITANIUM DIOXIDE 2.25 mL/50 mL

Drug Facts

Active Ingredients: ZINC OXIDE, TITANIUM DIOXIDE

Inactive ingredients:
WATER, CYCLOPENTASILOXANE, BUTYLENE GLYCOL, ETHYLHEXYL METHOXYCINNAMATE, PEG-10 DIMETHICONE, DIPROPYLENE GLYCOL, DIMETHICONE, CETYL ETHYLHEXANOATE, MAGNESIUM SULFATE, QUATERNIUM-18 HECTORITE, DIMETHICONE CROSSPOLYMER, DIMETHICONE/PEG-10/15 CROSSPOLYMER, PANTHENOL, PONCIRUS TRIFOLIATA FRUIT EXTRACT, PORTULACA OLERACEA EXTRACT, SORBITAN SESQUIOLEATE, ZINC STEARATE, DIMETHICONE/METHICONE COPOLYMER, ALUMINUM HYDROXIDE, STEARIC ACID, METHYLPARABEN, FRAGRANCE, DISTEARYLDIMONIUM CHLORIDE, VP/EICOSENE COPOLYMER, MICA, ACRYLATES/DIMETHICONE COPOLYMER, NYLON-12, DIPOTASSIUM GLYCYRRHIZATE, ETHYLPARABEN, PEG-9 POLYDIMETHYLSILOXYETHYL DIMETHICONE, IRON OXIDES(CI 77492), VINYL DIMETHICONE/METHICONE SILSESQUIOXANE CROSSPOLYMER, IRON OXIDES(CI 77491), TOCOPHERYL ACETATE, METHICONE, IRON OXIDES(CI 77499), TRIETHOXYCAPRYLYLSILANE, CAPRYLIC/CAPRIC TRIGLYCERIDE, ALCOHOL, GLYCERIN, ARGANIA SPINOSA KERNEL EXTRACT, RHEUM UNDULATUM ROOT/STALK/STEM EXTRACT, SODIUM COCOYL GLUTAMATE, CARBOMER, COPTIS CHINENSIS ROOT EXTRACT, CRAMBE MARITIMA EXTRACT

Warnings:
When using this product
Keep out of eyes. Rinse with water to remove.
Stop use and ask a doctor if
Rash or irritation develops and lasts.
Directions:
Apply evenly before sun exposure and as needed.
Children under 6months of age; ask a doctor.